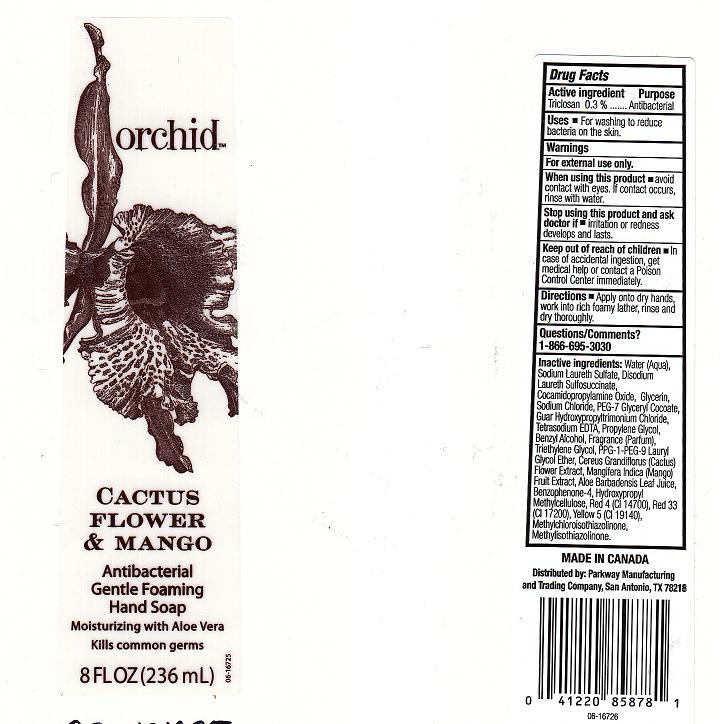 DRUG LABEL: CACTUS FLOWER AND MANGO ANTIBACTERIAL GENTLE FOAMING HAND SP
NDC: 37808-182 | Form: LIQUID
Manufacturer: HEB
Category: otc | Type: HUMAN OTC DRUG LABEL
Date: 20101229

ACTIVE INGREDIENTS: TRICLOSAN 0.3 mL/100 mL
INACTIVE INGREDIENTS: WATER; SODIUM LAURETH SULFATE; DISODIUM LAURETH SULFOSUCCINATE; COCAMIDOPROPYLAMINE OXIDE; GLYCERIN; SODIUM CHLORIDE; GLYCERYL COCOATE; GUAR GUM; EDETATE SODIUM; PROPYLENE GLYCOL; BENZYL ALCOHOL; TRIETHYLENE GLYCOL; POLIDOCANOL; SELENICEREUS GRANDIFLORUS FLOWER; MANGO; ALOE VERA LEAF; SULISOBENZONE; HYPROMELLOSES; FD&C RED NO. 4; D&C RED NO. 33; FD&C YELLOW NO. 5; METHYLCHLOROISOTHIAZOLINONE; METHYLISOTHIAZOLINONE

DRUG FACTS

ACTIVE INGREDIENT

TRICLOSAN 0.3 PERCENT

PURPOSE

ANTIBACTERIAL

USES

FOR WASHING TO REDUCE BACTERIA ON THE SKIN.

WARNINGS

FOR EXTERNAL USE ONLY.

WHEN USING THIS PRODUCT

AVOID CONTACT WITH EYES.IF CONTACT OCCURS, RINSE WITH WATER.

STOP USING THIS PRODUCT AND ASK DOCTOR IF

IRRITATION OR REDNESS DEVELOPS AND LASTS.

KEEP OUT OF REACH OF CHILDREN

IN CASE OF ACCIDENTAL INGESTION, GET MEDICAL HELP OR CONTACT A POISON CONTROL CENTER IMMEDIATELY.

DIRECTIONS

APPLY ONTO DRY HANDS, WORK INTO RICH FOAMY LATHER, RINSE AND DRY THOROUGHLY.

QUESTIONS OR COMMENTS

1-866-695-3030

INACTIVE INGREDIENTS

WATER, SODIUM LAURETH SULFATE, DISODIUM LAURETH SULFOSUCCINATE, COCAMIDOPROPYLAMINE OXIDE,GLYCERIN, SODIUM CHLORIDE, PEG-7 GLYCERYL COCOATE, GUAR HYDROXYPROPYLTRIMONIUM CHLORIDE, TETRASODIUM EDTA, PROPYLENE GLYCOL, BENZYL ALCOHOL, FRAGRANCE, TRIETHYLENE GLYCOL, PPG-1-PEG-9 LAURYL GLYCOL ETHER, CEREUS GRANDIFLORUS (CACTUS) FLOWER EXTRACT, MANGIFERA INDICA (MANGO) FRUIT EXTRACT, ALOE BARBADENSIS LEAF JUICE, BENZOPHENONE-4, HYDROXYPROPYL METHYLCELLULOSE, RED 4 (CI 14700), RED 33 (CI 17200), YELLOW 5 (CI 19140), METHYLCHLOROISOTHIAZOLINONE, METHYLISOTHIAZOLINONE.